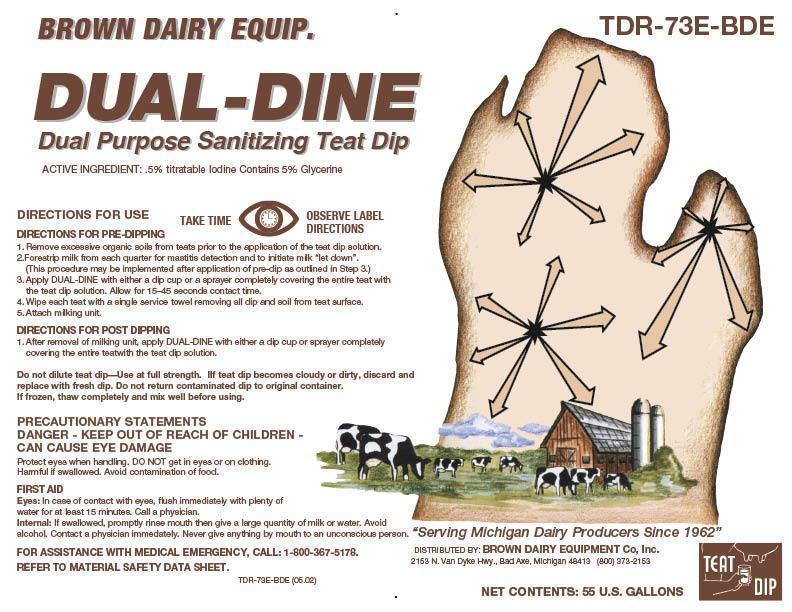 DRUG LABEL: DUAL-DINE
NDC: 62897-730 | Form: SOLUTION
Manufacturer: Brown Dairy Equipment
Category: animal | Type: OTC ANIMAL DRUG LABEL
Date: 20130108

ACTIVE INGREDIENTS: IODINE 5 g/1 L

DUAL-DINE

BROWN DAIRY EQUIP.

DUAL-DINE

Dual Purpose Sanitizing Teat Dip

ACTIVE INGREDIENT: 0.5% titratable iodine Contains 5% Glycerine

DIRECTIONS FOR USE

DIRECTIONS FOR PRE-DIPPING

1. Remove excessive organic soils from teats prior to the application of teat dip solution.
2. Forestrip milk from each quarter for mastitis detection and to initiate milk “let down”. (This procedure may be implemented after application of pre-dip as outlined in Step 3.)
3. Apply DUAL-DINE with either a dip cup or a sprayer completely covering the entire teat with the teat dip solution. Allow 15-45 seconds of contact time.
4. Wipe each teat with a single service towel removing all dip and soil from teat surface.
5. Attach milking unit.

DIRECTIONS FOR POST DPPING

1. After removal of milking unit, apply DUAL-DINE with either a dip cup or sprayer completely covering the entire teat with the teat dip solution.

Do not dilute teat dip – Use at full strength. If teat dip becomes cloudy or dirty, discard and replace with fresh dip. Do not return contaminated dip to original container.

If frozen, thaw completely and mix well before using.

PRECAUTIONARY STATEMENTS

DANGER - KEEP OUT OF REACH OF CHILDREN - CAN CAUSE EYE DAMAGE.

Protect eyes when handling. DO NOT get in eyes or on clothing. Harmful is swallowed. Avoid contamination of food.

FIRST AID

Eyes: In case of contact with eyes, flush immediately with plenty of water for at least 15 minutes. Call a physician.

Internal: If swallowed, promptly rinse mouth with water then give a large quantity of milk or water. Avoid alcohol. Contact a physician immediately. Never give anything by mouth to an unconscious person.

FOR ASSISTANCE WITH MEDICAL EMERGENCY, CALL 1-800-367-5178

REFER TO MATERIAL DATA SAFETY SHEET.

PRINCIPAL DISPLAY PANEL/REPRESENTATIVE LABEL

BROWN DAIRY EQUIP.

DUAL-DINE

Dual Purpose Sanitizing Teat Dip

ACTIVE INGREDIENT: 0.5% titratable iodine Contains 5%Glycerine

TAKE TIME OBSERVE LABEL DIRECTIONS

“Serving Michigan Dairy Producers Since 1962”

Distributed by: Brown Dairy Equipment

2152 N. Van Dyke Rd., Bad Axe, Michigan 48413 (800) 373-2153

NET CONTENTS: 55 U.S. GALLONS